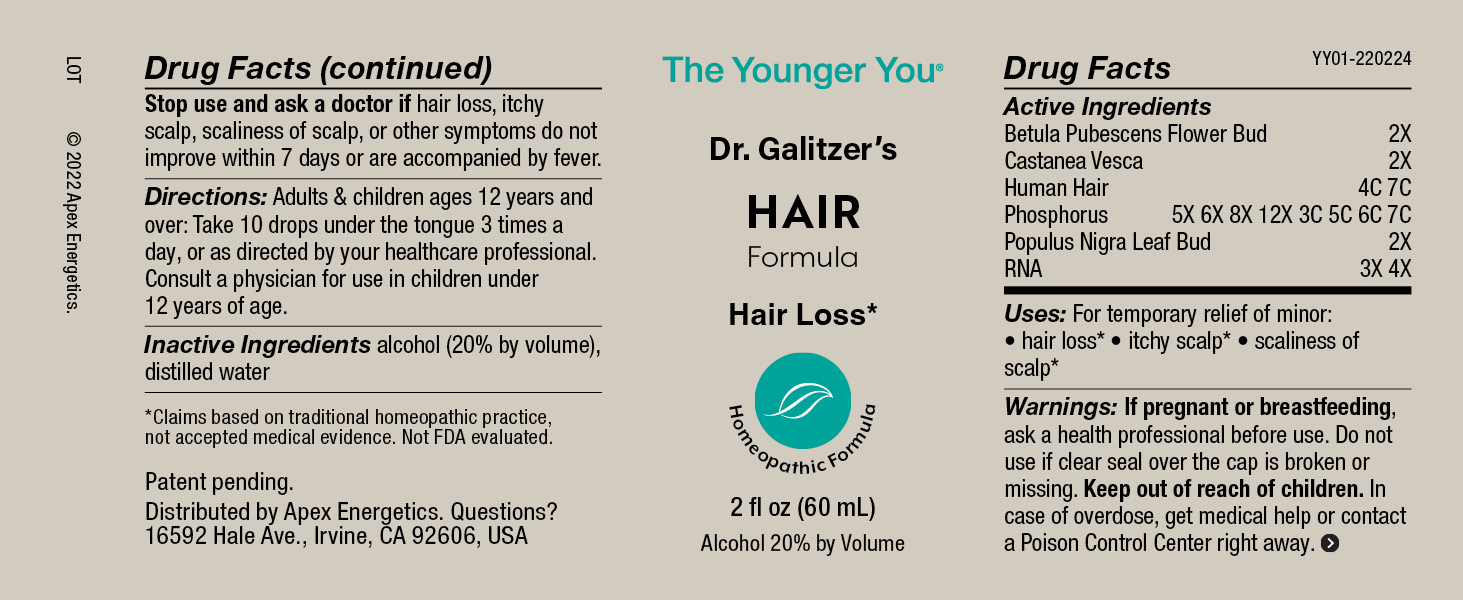 DRUG LABEL: HAIR Formula
NDC: 63479-2501 | Form: SOLUTION/ DROPS
Manufacturer: Apex Energetics Inc.
Category: homeopathic | Type: HUMAN OTC DRUG LABEL
Date: 20240108

ACTIVE INGREDIENTS: PHOSPHORUS 7 [hp_C]/1 mL; POPULUS NIGRA LEAF BUD 2 [hp_X]/1 mL; SACCHAROMYCES CEREVISIAE RNA 4 [hp_X]/1 mL; BETULA PUBESCENS FLOWER BUD 2 [hp_X]/1 mL; HUMAN HAIR 7 [hp_C]/1 mL; CASTANEA SATIVA LEAF 2 [hp_X]/1 mL
INACTIVE INGREDIENTS: WATER; ALCOHOL

YY01

Active Ingredients
Betula Pubescens Flower Bud | 2X
Castanea Vesca | 2X
Human Hair | 4C 7C
Phosphorus | 5X 6X 8X 12X 3C 5C 6C 7C
Populus Nigra Leaf Bud | 2X
RNA | 3X 4X

INDICATIONS AND USAGE

Uses:

For temporary relief of minor:

hair loss*

itchy scalp*

scaliness of scalp*

*Claims based on traditional homeopathic practice, not accepted medical evidence. Not FDA evaluated.

Warnings:

PREGNANCY OR BREAST FEEDING

If pregnant or breastfeeding, ask a health professional before use.

Do not use if clear seal over the cap is broken or missing.

Keep out of reach of children. In case of overdose, get medical help or contact a Poison Control Center right away.

Stop use and ask a doctor if hair loss, itchy scalp, scaliness of scalp, or other symptoms do not improve within 7 days or are accompanied by fever.

Directions:

Adults & children ages 12 years and over: Take 10 drops under the tongue 3 times a day, or as directed by your healthcare professional. Consult a physician for use in children under 12 years of age.

Inactive Ingredients

alcohol (20% by volume), distilled water

Distributed by Apex Energetics. Questions?
16592 Hale Ave., Irvine, CA 92606, USA

PACKAGE LABEL

The Younger You®

Dr. Galitzer’s

HAIR

Formula

Hair Loss*

Homeopathic Formula

2 fl oz (60 mL)

Alcohol 20% by Volume